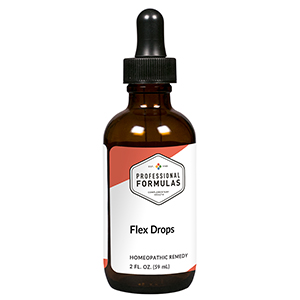 DRUG LABEL: Flex Drops
NDC: 63083-2024 | Form: LIQUID
Manufacturer: Professional Complementary Health Formulas
Category: homeopathic | Type: HUMAN OTC DRUG LABEL
Date: 20190815

ACTIVE INGREDIENTS: ANGELICA ARCHANGELICA ROOT 2 [hp_X]/59 mL; ANGELICA PUBESCENS ROOT 2 [hp_X]/59 mL; GAMBIR 2 [hp_X]/59 mL; MAGNESIUM PHOSPHATE, DIBASIC TRIHYDRATE 2 [hp_X]/59 mL; GUAIAC 3 [hp_X]/59 mL; POTASSIUM CHLORIDE 3 [hp_X]/59 mL; MANGANESE 3 [hp_X]/59 mL; YUCCA FILAMENTOSA WHOLE 3 [hp_X]/59 mL; BRYONIA ALBA ROOT 6 [hp_X]/59 mL; BOVINE TYPE II COLLAGEN (TRACHEAL CARTILAGE) 6 [hp_X]/59 mL; CAUSTICUM 6 [hp_X]/59 mL; RHODODENDRON TOMENTOSUM LEAFY TWIG 6 [hp_X]/59 mL; TOXICODENDRON PUBESCENS LEAF 6 [hp_X]/59 mL; RUTA GRAVEOLENS FLOWERING TOP 6 [hp_X]/59 mL; LATIGLUTENASE 8 [hp_X]/59 mL; OXALIC ACID 8 [hp_X]/59 mL; ARNICA MONTANA WHOLE 8 [hp_X]/59 mL; LATRODECTUS MACTANS 10 [hp_X]/59 mL
INACTIVE INGREDIENTS: ALCOHOL; WATER

C24

ACTIVE INGREDIENTS

Angelica archangelica 2X
Du huo 2X
Shujin chin 2X
Magnesia phosphorica 2X, 3X, 6X
Guaiacum 3X
Kali muriaticum 3X
Manganum metallicum 3X
Yucca filamentosa 3X
Bryonia 6X
Cartilage 6X
Causticum 6X
Ledum palustre 6X
Rhus toxicodendron 6X
Ruta graveolens 6X
Hordeum vulgare 8X
Oxalicum acidum 8X, 12X
Arnica montana 8X, 100X, 1000X
Latrodectus mactans 10X

QUESTIONS

Professional Formulas

PO Box 2034 Lake Oswego, OR 97035

INDICATIONS

For the temporary relief of pain or stiffness in joints, tendons, or muscles.*

PURPOSE

*Claims based on traditional homeopathic practice, not accepted medical evidence. Not FDA evaluated.

WARNINGS

In case of overdose, get medical help or contact a poison control center right away.

Keep out of the reach of children.

PREGNANCY OR BREAST FEEDING

If pregnant or breastfeeding, ask a healthcare professional before use.

DIRECTIONS

Place drops under tongue 30 minutes before/after meals. Adults and children 12 years and over: Take 10 drops up to 3 times per day for up to 6 weeks. For immediate onset of symptoms, take 10 to 15 drops every 15 minutes up to 3 hours. For less severe symptoms, take 10-15 drops hourly up to 8 hours. Consult a physician for use in children under 12 years of age.

OTHER INFORMATION

Tamper resistant. If seal is broken, do not use. After opening, close container tightly and store at room temperature away from heat.

INACTIVE INGREDIENTS

20% ethanol, purified water.

LABEL

Est 1985

Professional Formulas

Complementary Health

Flex Drops

Homeopathic Remedy

2 FL. OZ. (59 mL)